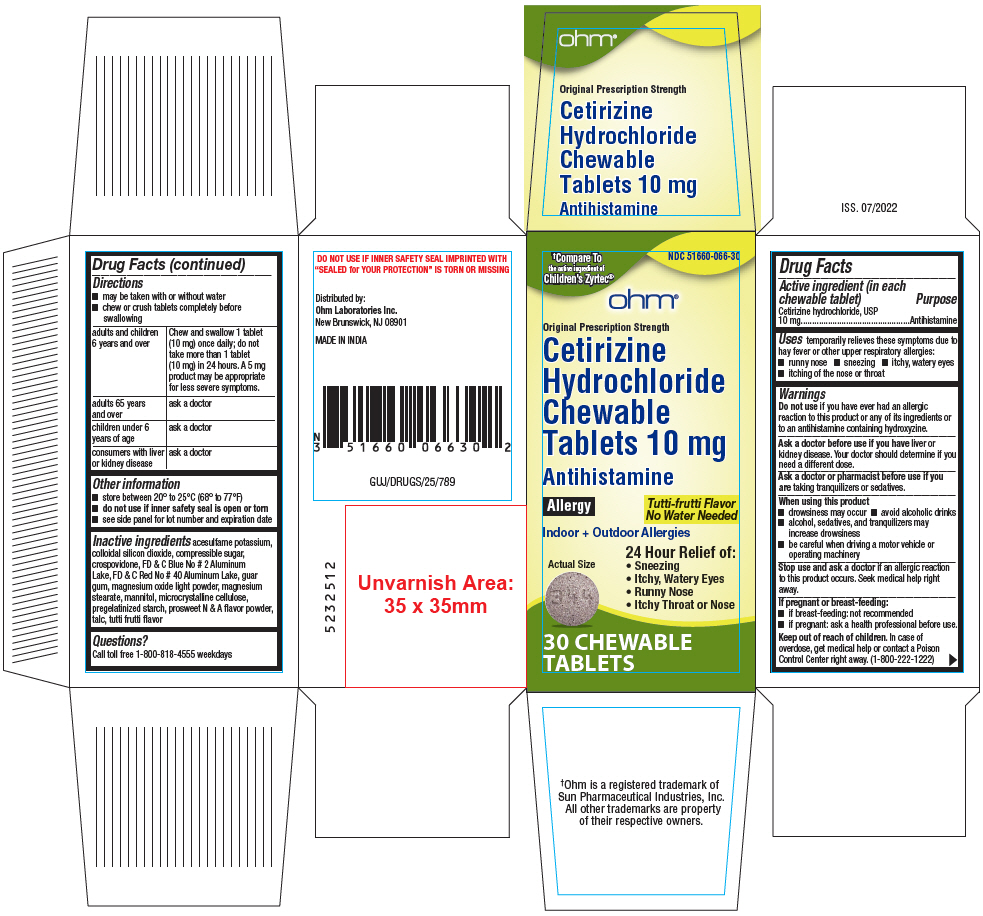 DRUG LABEL: Cetirizine Hydrochloride
NDC: 51660-066 | Form: TABLET, CHEWABLE
Manufacturer: OHM LABORATORIES INC.
Category: otc | Type: HUMAN OTC DRUG LABEL
Date: 20220726

ACTIVE INGREDIENTS: CETIRIZINE HYDROCHLORIDE 10 mg/1 1
INACTIVE INGREDIENTS: ACESULFAME POTASSIUM; SILICON DIOXIDE; SUCROSE; CROSPOVIDONE (120 .MU.M); FD&C BLUE NO. 2; FD&C RED NO. 40; GUAR GUM; MAGNESIUM OXIDE; MAGNESIUM STEARATE; MANNITOL; MICROCRYSTALLINE CELLULOSE; STARCH, CORN; TALC

Cetirizine Hydrochloride

Drug Facts

Active ingredient (in each chewable tablet)

Cetirizine hydrochloride, USP 10 mg

Purpose

Antihistamine

Uses

temporarily relieves these symptoms due to hay fever or other upper respiratory allergies:

- runny nose
- sneezing
- itchy, watery eyes
- itching of the nose or throat

Warnings

Do not use if you have ever had an allergic reaction to this product or any of its ingredients or to an antihistamine containing hydroxyzine.

Ask a doctor before use if you have liver or kidney disease. Your doctor should determine if you need a different dose.

Ask a doctor or pharmacist before use if you are taking tranquilizers or sedatives.

When using this product

- drowsiness may occur
- avoid alcoholic drinks
- alcohol, sedatives, and tranquilizers may increase drowsiness
- be careful when driving a motor vehicle or operating machinery

Stop use and ask a doctor if an allergic reaction to this product occurs. Seek medical help right away.

If pregnant or breast-feeding

- if breast-feeding: not recommended
- if pregnant: ask a health professional before use.

Keep out of reach of children. In case of overdose, get medical help or contact a Poison Control Center right away. (1-800-222-1222)

Directions

- may be taken with or without water
- chew or crush tablets completely before swallowing

adults and children 6 years and over | Chew and swallow 1 tablet (10 mg) once daily; do not take more than 1 tablet (10 mg) in 24 hours. A 5 mg product may be appropriate for less severe symptoms.
adults 65 years and over | ask a doctor
children under 6 years of age | ask a doctor
consumers with liver or kidney disease | ask a doctor

Other information

- store between 20° to 25°C (68° to 77°F)
- do not use if inner safety seal is open or torn
- see side panel for lot number and expiration date

Inactive ingredients

acesulfame potassium, colloidal silicon dioxide, compressible sugar, crospovidone, FD & C Blue No # 2 Aluminum Lake, FD & C Red No # 40 Aluminum Lake, guar gum, magnesium oxide light powder, magnesium stearate, mannitol, microcrystalline cellulose, pregelatinized starch, prosweet N & A flavor powder, talc, tutti frutti flavor

Questions?

Call toll free 1-800-818-4555 weekdays

Distributed by:
Ohm Laboratories Inc.
New Brunswick, NJ 08901

PRINCIPAL DISPLAY PANEL - 10 mg Tablet Bottle Carton

†Compare To
the active ingredient of
Children's Zyrtec®

NDC 51660-066-30

ohm®

Original Prescription Strength

Cetirizine
Hydrochloride
Chewable
Tablets 10 mg

Antihistamine

Allergy

Tutti-frutti Flavor
No Water Needed

Indoor + Outdoor Allergies

Actual Size

24 Hour Relief of:

- Sneezing
- Itchy, Watery Eyes
- Runny Nose
- Itchy Throat or Nose

30 CHEWABLE
TABLETS